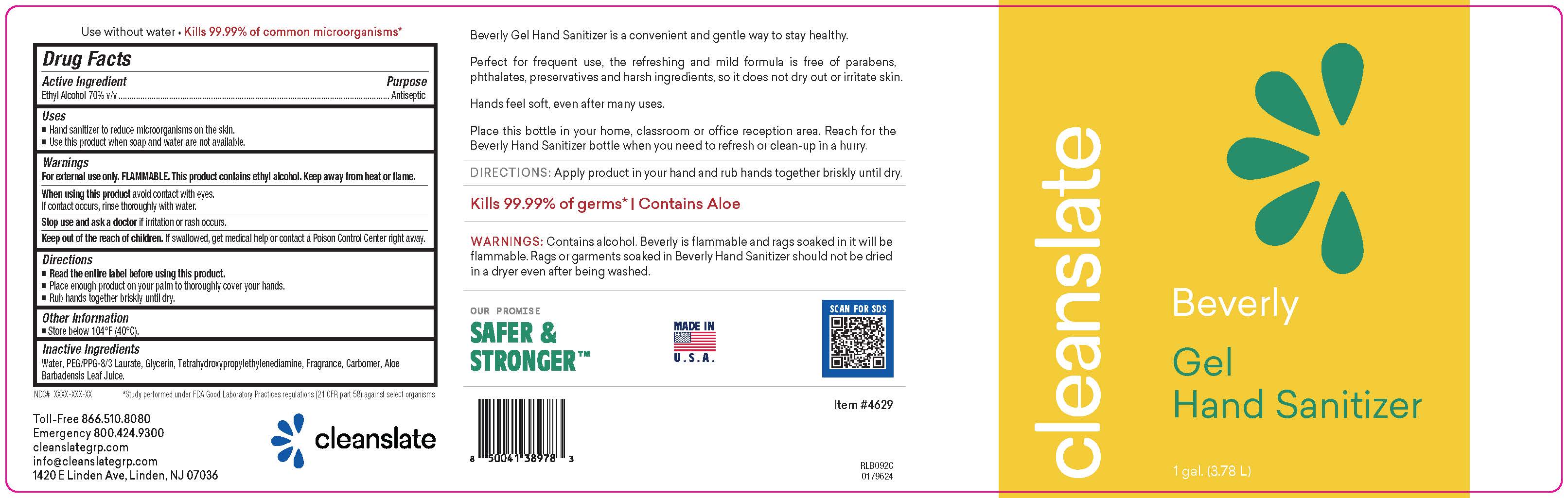 DRUG LABEL: Beverly Gel Hand Sanitizer
NDC: 80586-801 | Form: GEL
Manufacturer: Cleanslate Group LLC
Category: otc | Type: HUMAN OTC DRUG LABEL
Date: 20251008

ACTIVE INGREDIENTS: ALCOHOL 0.7 mL/1 mL
INACTIVE INGREDIENTS: DIMETHICONE PEG-8 LAURATE 0.013 mL/1 mL; EDETOL 0.0035 mL/1 mL; GLYCERIN 1 mL/1 mL; FRAGRANCE LEMON ORC2001060 0.0003 mL/1 mL; CARBOMER INTERPOLYMER TYPE A (ALLYL SUCROSE CROSSLINKED) 0.0035 mL/1 mL; ALOE VERA LEAF 0.00001 mL/1 mL; WATER 0.3 mL/1 mL

Beverly Gel Hand Sanitizer

Acive Ingredient

ethyl Alcohol

inactive ingredients

Water

Carbomer

Dimethicone PEG-8 Laurate

Glycerin

EDETOL

Fragrance

Aloe Barbadensis Leaf Juice

dosage

Place enough product on your palm to thoroughly cover your hands

Rub hands together brisky until dry

indications

Hand sanitizer to reduce microorganisms on skin

Use this product when soap and water are not available

purpose

Antiseptic

Keep out of reach of children. If swallowed get medical help or contact a Poison Control center right away

warnings

For external use only. FLAMMABLE. This product contains ethyl alcohol. Keep away from flame

When using this product avoid contact with eyes.

Stop use and ask doctor if irritaiton or rash occurs.